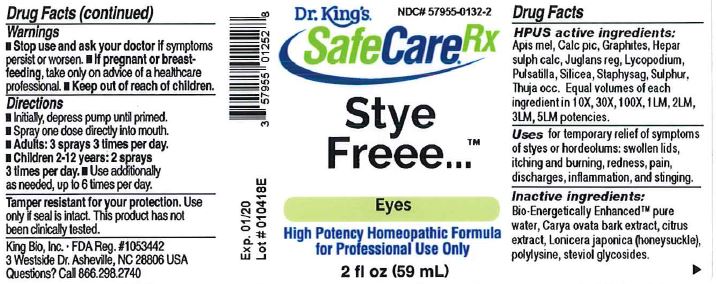 DRUG LABEL: Stye Freee
NDC: 57955-0132 | Form: LIQUID
Manufacturer: King Bio Inc.
Category: homeopathic | Type: HUMAN OTC DRUG LABEL
Date: 20180219

ACTIVE INGREDIENTS: APIS MELLIFERA 10 [hp_X]/59 mL; CALCIUM PICRATE 10 [hp_X]/59 mL; GRAPHITE 10 [hp_X]/59 mL; CALCIUM SULFIDE 10 [hp_X]/59 mL; JUGLANS REGIA FRUIT RIND, IMMATURE 10 [hp_X]/59 mL; LYCOPODIUM CLAVATUM SPORE 10 [hp_X]/59 mL; PULSATILLA VULGARIS 10 [hp_X]/59 mL; SILICON DIOXIDE 10 [hp_X]/59 mL; DELPHINIUM STAPHISAGRIA SEED 10 [hp_X]/59 mL; SULFUR 10 [hp_X]/59 mL; THUJA OCCIDENTALIS LEAFY TWIG 10 [hp_X]/59 mL
INACTIVE INGREDIENTS: WATER; CARYA OVATA BARK; CITRUS BIOFLAVONOIDS; LONICERA JAPONICA FLOWER; POLYEPSILON-LYSINE (4000 MW); REBAUDIOSIDE A

Stye Freee™

ACTIVE INGREDIENT

Drug Facts__________________________________________________________________________________________________________

HPUS active ingredients:

Apis mel, Calc pic, Graphites, Hepar sulph calca, Juglans reg, Lycopodium, Pulsatilla, Silicea, Staphysag, Sulphur, Thuja occ.

Equal volumes of each ingredient in 10X, 30X, 100X, 1LM, 2LM, 3LM, 5LM potencies.

INDICATIONS AND USAGE

Uses for temporary relief of symptoms of styes or hordeolums: swollen lids, itching and burning, redness, pain, discharges, inflammation, and stinging.

Inactive Ingredients:

Bio-Energetically Enhanced™ pure water, Carya ovata bark extract, citrus extract, Lonicera japonica (honeysuckle), polylysine, steviol glycosides.

Warnings

- Stop use and ask your doctor if symptoms persist or worsen.
- If pregnant or breast-feeding, take only on advice of a healthcare professional.

- Keep out of reach of children.

Directions

- Initially, depress pump until primed.
- Spray one dose directly into mouth.
- Adults: 3 sprays 3 times per day.
- Children 2-12 years: 2 sprays 3 times per day.
- Use additionally as needed, up to 6 times per day.

OTHER SAFETY INFORMATION

Tamper resistant for your protection. Use only if safety seal is intact. This product has not been clinically tested.

PURPOSE

Uses for temporary relief of symptoms of styes or hordeolums:

- swollen lids
- itching and burning
- redness
- pain
- discharges
- inflammation
- stinging